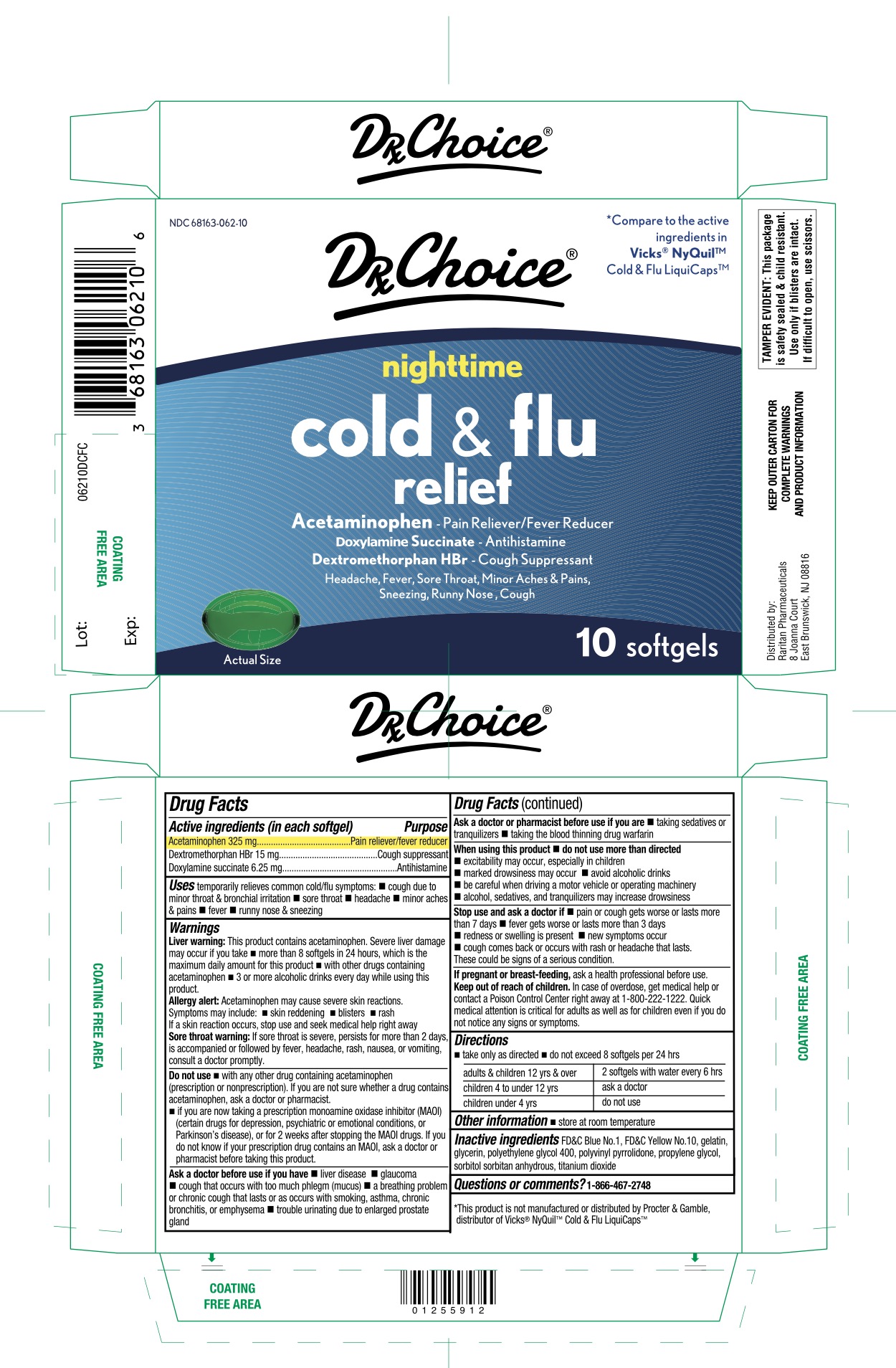 DRUG LABEL: DRX CHOICE
NDC: 68163-062 | Form: CAPSULE, LIQUID FILLED
Manufacturer: Raritan Pharmaceuticals Inc.
Category: otc | Type: HUMAN OTC DRUG LABEL
Date: 20260121

ACTIVE INGREDIENTS: ACETAMINOPHEN 325 mg/1 1; DEXTROMETHORPHAN HYDROBROMIDE 15 mg/1 1; DOXYLAMINE SUCCINATE 6.25 mg/1 1
INACTIVE INGREDIENTS: FD&C BLUE NO. 1; D&C YELLOW NO. 10; GELATIN, UNSPECIFIED; GLYCERIN; POLYETHYLENE GLYCOL, UNSPECIFIED; POVIDONE, UNSPECIFIED; PROPYLENE GLYCOL; SORBITOL; TITANIUM DIOXIDE

DRx Choice® nighttime cold & Flu

Drug Facts

Active ingredients (in each softgel)

Acetaminophen 325 mg
Dextromethorphan HBr 15 mg
Doxylamine succinate 6.25 mg

Purpose

Pain reliever/fever reducer

Cough suppressant

Antihistamine

Uses

temporarily relieves common cold/flu symptoms:

- cough due to minor throat & bronchial irritation
- sore throat
- headache
- minor aches & pains
- fever
- runny nose & sneezing

Warnings

Liver warning: This product contains acetaminophen. Severe liver damage may occur if you take

- more than 8 softgels in 24 hours, which is the maximum daily amount for this product
- with other drugs containing acetaminophen • 3 or more alcoholic drinks every day while using this product

Allergy Alert: Acetaminophen may cause severe skin reactions. Symptoms may include:

- skin reddening
- blisters
- rash

If a skin reaction occurs, stop use and seek medical help right away
Sore throat warning: If sore throat is severe, persists for more than 2 days, is accompanied or followed by fever, headache, rash, nausea, or vomiting, consult a doctor promptly.

Do not use

- with any other drug containing acetaminophen (prescription or nonprescription). If you are not sure whether a drug contains acetaminophen, ask a doctor or pharmacist.
- if you are now taking a prescription monoamine oxidase inhibitor (MAOI) (certain drugs for depression, psychiatric or emotional conditions, or Parkinson's disease), or for 2 weeks after stopping the MAOI drug. If you do not know if your prescription drug contains an MAOI, ask a doctor or pharmacist before taking this product.

Ask a doctor before use if you have

- liver disease
- glaucoma
- cough that occurs with too much phlegm (mucus)
- a breathing problem or chronic cough that lasts or as occurs with smoking, asthma, chronic bronchitis or emphysema
- trouble urinating due to enlarged prostate gland

Ask a doctor or pharmacist before use if you are

- taking sedatives or tranquilizers
- taking the blood thinning drug warfarin

When using this product

- do not use more than directed
- excitability may occur, especially in children
- marked drowsiness may occur
- avoid alcoholic drinks
- be careful when driving a motor vehicle or operating machinery
- alcohol, sedatives, & tranquilizers may increase drowsiness

Stop use and ask a doctor if

- pain or cough gets worse or lasts more than 7 days
- fever gets worse or lasts more than 3 days
- redness or swelling is present
- new symptoms occur
- cough comes back or occurs with rash or headache that lasts. These could be signs of a serious condition.

PREGNANCY OR BREAST FEEDING

If pregnant or breast-feeding, ask a health professional before use.

Keep out of reach of children.

In case of overdose, get medical help or contact a Poison Control Center right away. Quick medical attention is critical for adults as well as for children even if you do not notice any signs or symptoms.

Directions

- take only as directed
- do not exceed 8 softgels per 24 hrs

adults & children 12 yrs & over | 2 softgels with water every 6 hrs
children 4 to under 12 yrs | ask a doctor
children under 4 yrs | do not use

Other information

- store at room temperature

Inactive ingredients

FD&C Blue No. 1, D&C Yellow No. 10, gelatin, glycerin, polyethylene glycol 400, polyvinyl pyrrolidone, propylene glycol, sorbitol sorbitan anhydrous, titanium dioxide

Questions or comments?

1-866-467-2748

TAMPER EVIDENT: This package is safety-sealed & child resistant. Use only if blisters are intact. If difficult to open, use scissors.

Distributed by:
Raritan Pharmaceuticals
8 Joanna Court

East Brunswick, NJ 08816

PRINCIPAL DISPLAY PANEL

*Compare to the active ingredients in Vicks® NyQuil™ Cold & Flu LiquiCaps™

DRx Choice®

Nighttime

Cold & flu relief

Acetaminophen – Pain Reliever/Fever Reducer

Doxylamine Succinate – Antihistamine

Dextromethorphan HBr – Cough Suppressant

Headache, Fever, Sore Throat, Minor Aches & Pains

Sneezing, Runny Nose, Cough

10 softgels